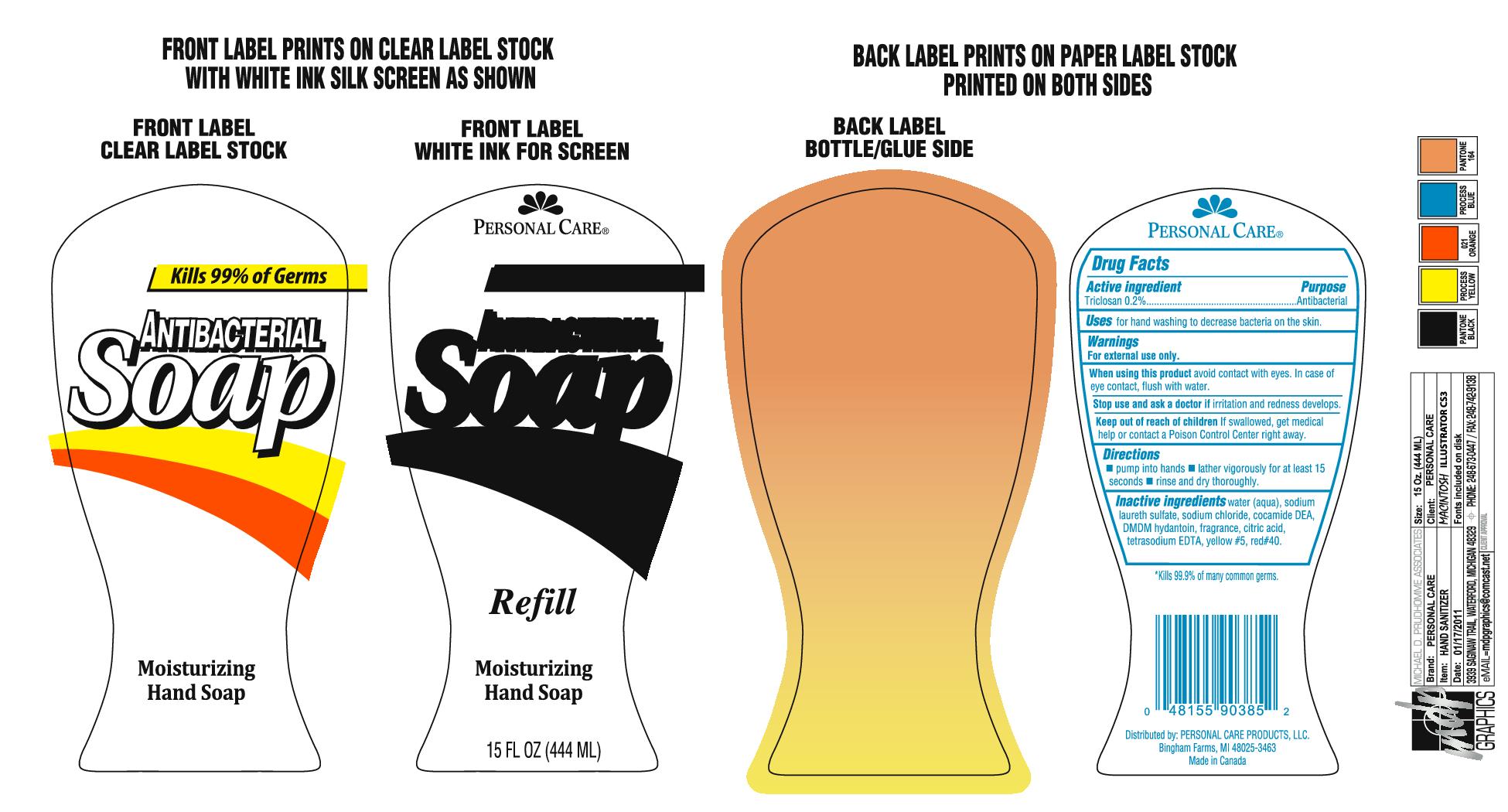 DRUG LABEL: Antibacterial
                        
NDC: 29500-903 | Form: SOAP
Manufacturer: Personal Care Products LLC
Category: otc | Type: HUMAN OTC DRUG LABEL
Date: 20111026

ACTIVE INGREDIENTS: TRICLOSAN .888 mL/444 mL
INACTIVE INGREDIENTS: WATER; SODIUM LAURETH SULFATE; SODIUM CHLORIDE; COCO DIETHANOLAMIDE; DMDM HYDANTOIN; CITRIC ACID MONOHYDRATE; EDETATE SODIUM; FD&C YELLOW NO. 5

Antibacterial

Active Ingredient

Triclosan 0.2%

Purpose antibacterial

Keep out of reach of children If swallowed, get medical help or contact a Poison Control Center right away.

Uses

for hand washing to decrease bacteria on the skin.

Warnings

For external use only.

When using this product avoid contact with eyes. In case of eye contact, flush with water.

Stop use and ask a doctor if irritation and redness develops.

Directions

Pump into hands

Lather vigorously for at least 15 seconds

Rinse and dry thoroughly

Inactive ingredients

Water (aqua), sodium laureth sulfate, sodium chloride, coamide DEA, DMDM hydantoin, fragrance, citric acid, tetrasodium EDTA, yellow #5, red #40

PACKAGE LABEL

Kills 99% of germs

Antibacterial soap

Moisterizing hand soap

15 fl oz (444 ml)